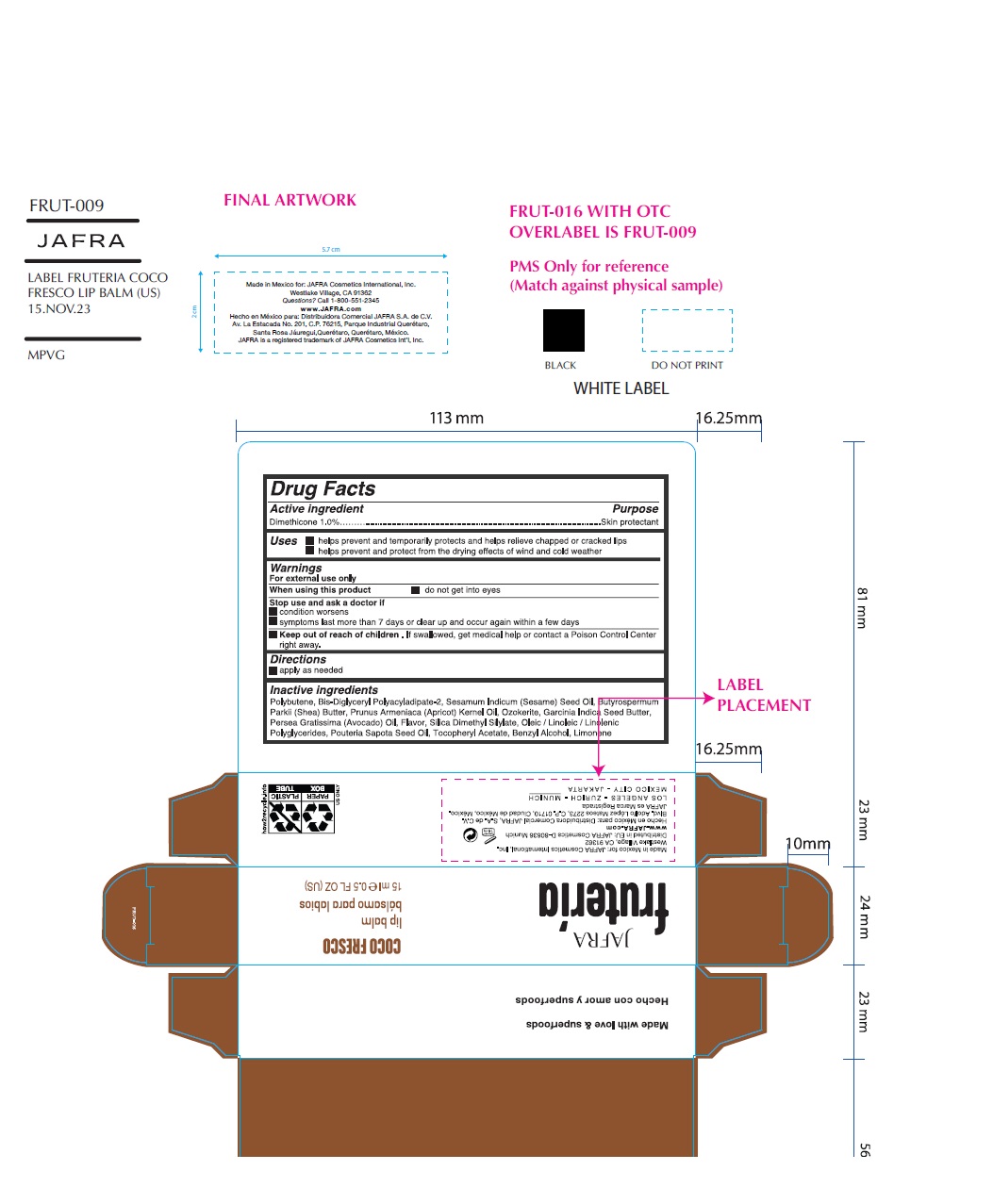 DRUG LABEL: JAFRA Fruteria Coco Fresco Lip Balm
NDC: 68828-010 | Form: GEL
Manufacturer: Distribuidora Comercial Jafra, S.A. de C.V.
Category: otc | Type: HUMAN OTC DRUG LABEL
Date: 20251021

ACTIVE INGREDIENTS: DIMETHICONE 1 g/100 mL
INACTIVE INGREDIENTS: POLYBUTENE (1400 MW); BIS-DIGLYCERYL POLYACYLADIPATE-2; SESAME OIL; SHEA BUTTER; APRICOT KERNEL OIL; CERESIN; GARCINIA INDICA SEED BUTTER; AVOCADO OIL; SILICA DIMETHYL SILYLATE; .ALPHA.-TOCOPHEROL ACETATE; BENZYL ALCOHOL; LIMONENE, (+)-; POUTERIA SAPOTA WHOLE

Active Ingredient

Dimethicone 1%

Purpose

Skin protectant

Uses

- Helps prevent and temporarily protects and helps relieve chapped or cracked lips
- Helps prevent and protect from the drying effects of wind and cold weather

Warnings

For external use only
When using this product● do not get into eyes
Stop use and ask a doctor if● condition worsens ● symptoms last more than 7 days or clear up and occur again in a few days
Keep out of reach of children. If swallowed, get medical help or contact a Poison Control Center right away.

Directions

• apply as needed

Inactive Ingredients

Polybutene, Bis-Diglyceryl Polyacyladipate-2, Sesamum Indicum (Sesame) Seed Oil, Butyrospermum Parkii (Shea) Butter, Prunus Armeniaca (Apricot) Kernel Oil, Ozokerite, Garcinia Indica Seed Butter, Persea Gratissima (Avocado) Oil, Flavor, Silica Dimethyl Silylate, Oleic / Linoleic / Linolenic Polyglycerides, Pouteria Sapota Seed Oil, Tocopheryl Acetate, Benzyl Alcohol, Limonene.